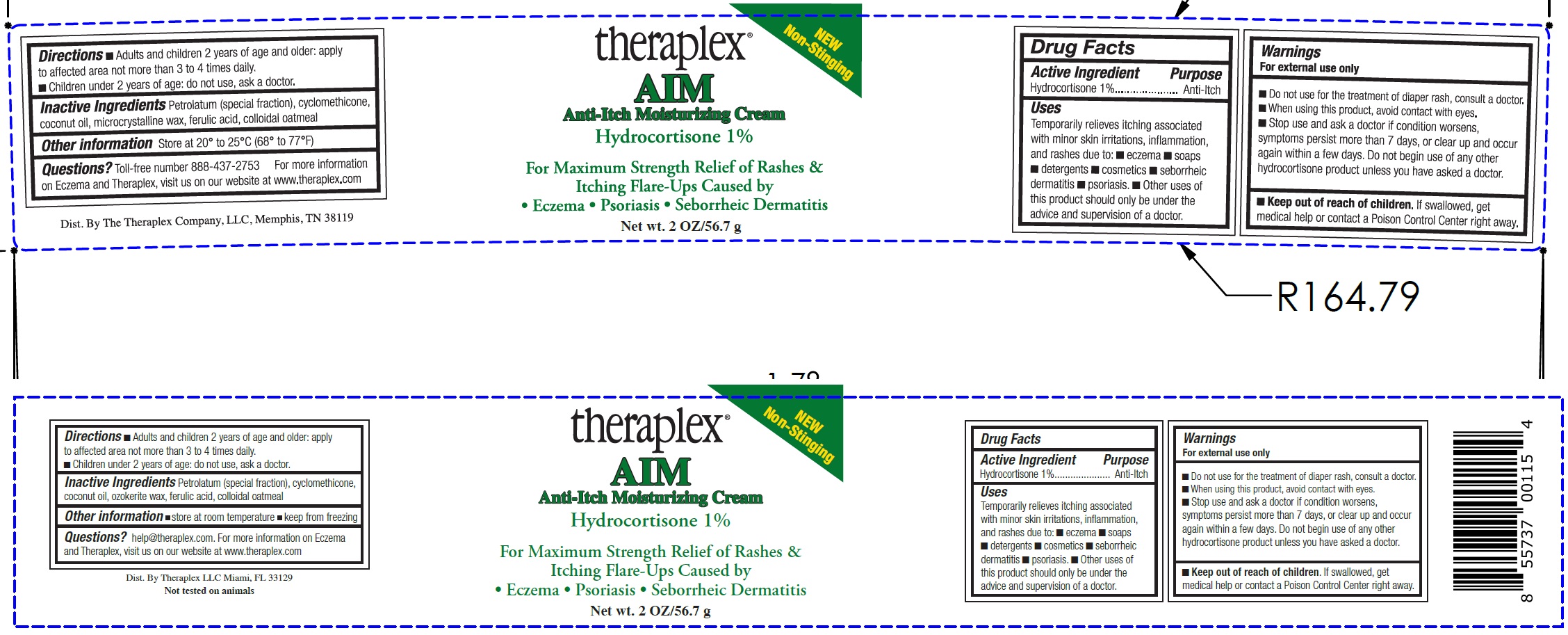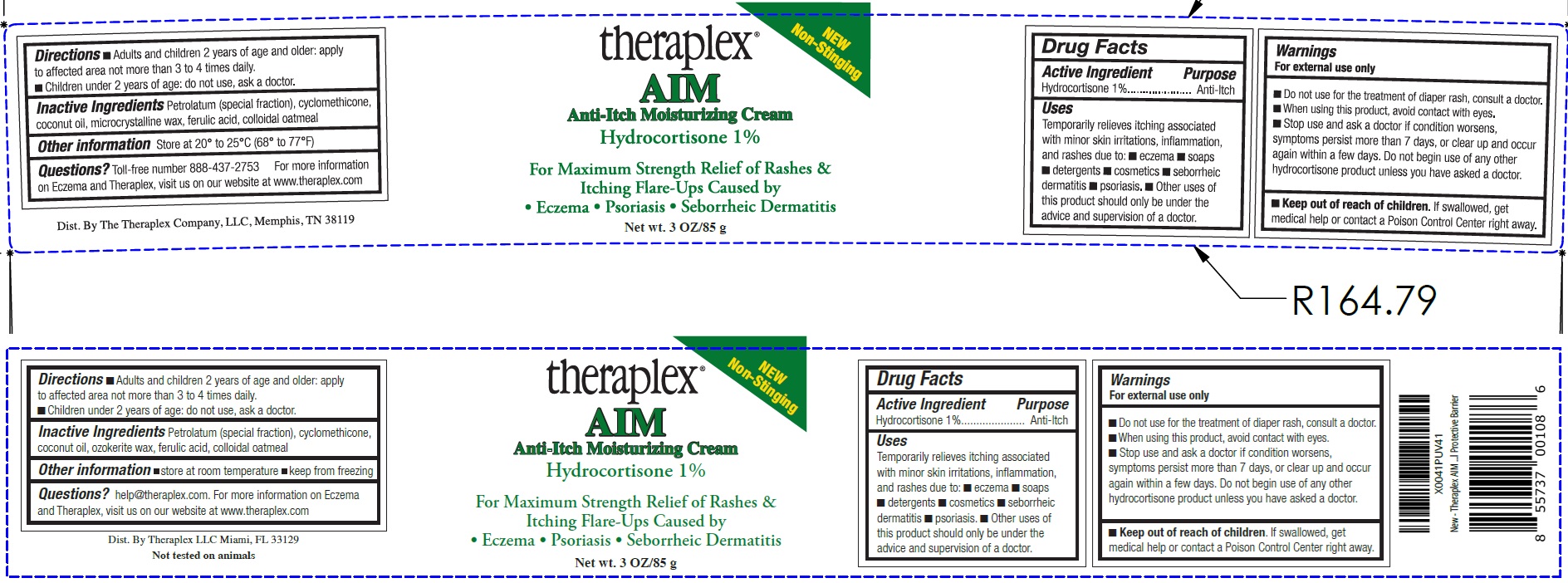 DRUG LABEL: THERAPLEX AIM Anti-Itch Moisturizing
NDC: 82280-478 | Form: CREAM
Manufacturer: THERAPLEX, LLC
Category: otc | Type: HUMAN OTC DRUG LABEL
Date: 20240427

ACTIVE INGREDIENTS: HYDROCORTISONE 10 mg/1 g
INACTIVE INGREDIENTS: PETROLATUM; CYCLOMETHICONE; COCONUT OIL; MICROCRYSTALLINE WAX; FERULIC ACID; OATMEAL

THERAPLEX AIM Anti-Itch Moisturizing Cream

Active Ingredient

Hydrocortisone 1%

Purpose

Anti-Itch

Uses

Temporarily relieves itching associated with minor skin irritations, inflammation, and rashes due to:

- eczema
- soaps
- detergents
- cosmetics
- seborrheic dermatitis
- psoriasis.
- Other uses of this product should only be under the advice and supervision of a doctor.

Warnings

For external use only

Do not use

- for the treatment of diaper rash, consult a doctor.

When using this product,

- avoid contact with eyes.

Stop use and ask a doctor if

- condition worsens, symptoms persist more than 7 days, or clear up and occur again within a few days. Do not begin use of any other hydrocortisone product unless you have asked a doctor.

Keep out of reach of children.

- If swallowed, get medical help or contact a Poison Control Center right away.

Directions

- Adults and children 2 years of age and older: apply to affected area not more than 3 to 4 times daily.
- Children under 2 years of age: do not use, ask a doctor.

Inactive Ingredients

Petrolatum (special fraction), cyclomethicone, coconut oil, microcrystalline wax, ferulic acid, colloidal oatmeal

Other information

- Store at 20° to 25°C (68° to 77°F)

Questions?

Toll-free number 888-437-2753 For more information on Eczema and Theraplex, visit us on our website at www.theraplex.com